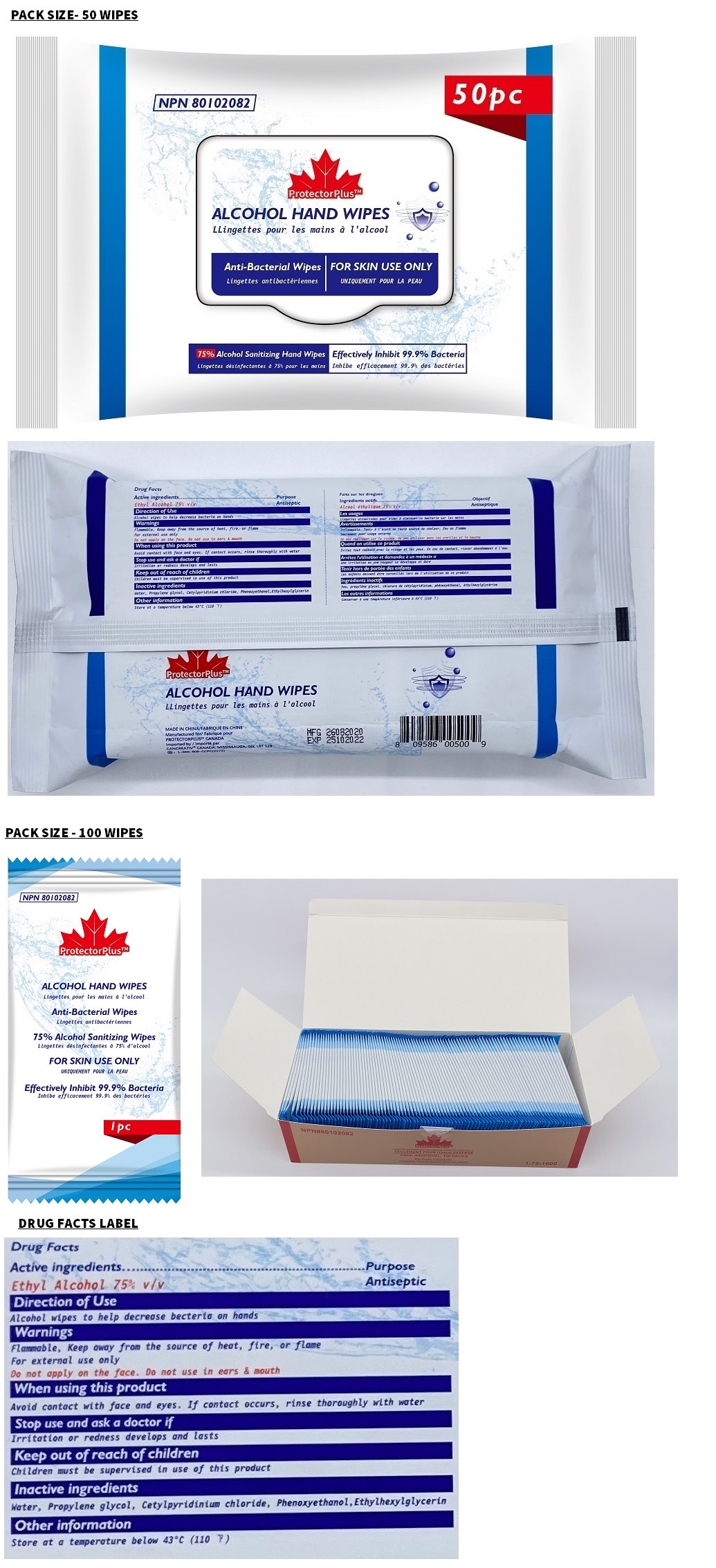 DRUG LABEL: ProtectorPlus ALCOHOL HAND WIPES
NDC: 78378-666 | Form: CLOTH
Manufacturer: Cancreativ Packing Corp
Category: otc | Type: HUMAN OTC DRUG LABEL
Date: 20210405

ACTIVE INGREDIENTS: ALCOHOL 75 mL/100 mL
INACTIVE INGREDIENTS: WATER; PROPYLENE GLYCOL; CETYLPYRIDINIUM CHLORIDE; PHENOXYETHANOL; ETHYLHEXYLGLYCERIN

ProtectorPlus™ ALCOHOL HAND WIPES

Active ingredients

Ethyl Alcohol 75% v/v

Purpose

Antiseptic

Direction of Use

Alcohol wipes to help decrease bacteria on hands

Warnings

Flammable, Keep away from the source of heat, fire, or flame
For external use only
Do not apply on the face. Do not use in ears & mouth

When using this product
Avoid contact with face and eyes. If contact occurs, rinse thoroughly with water

Stop use and ask a doctor if
Irritation or redness develops and lasts

Keep out of reach of children
Children must be supervised in use of this product

Directions

Wet hands thoroughly with product and allow to dry without wiping

Other information

Store at a temperature below 43°C (110 °F)

Inactive ingredients

Water, Propylene glycol, Cetylpyridinium chloride, Phenoxyethanol, Ethylhexylglycerin

Anti-Bacterial Wipes

FOR SKIN USE ONLY

Effectively Inhibit 99.9% Bacteria

MADE IN CHINA
Manufactured for
PROTECTORPLUS™ CANADA

Imported by
CANCREATIV® CANADA, MISSISSAUGA, ON, L5T 1Z9
1-866-808-CCPC(2272)